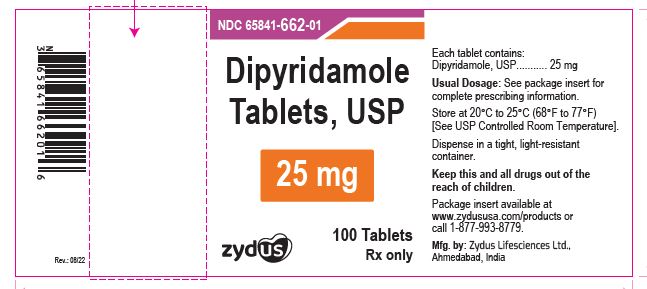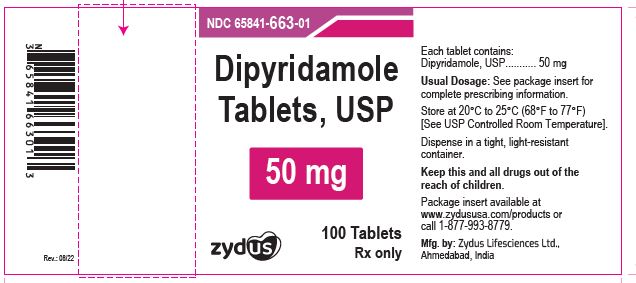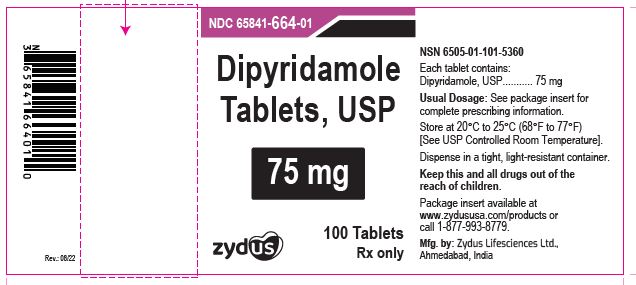 DRUG LABEL: Dipyridamole
NDC: 65841-662 | Form: TABLET, FILM COATED
Manufacturer: Zydus Lifesciences Limited
Category: prescription | Type: HUMAN PRESCRIPTION DRUG LABEL
Date: 20241126

ACTIVE INGREDIENTS: DIPYRIDAMOLE 25 mg/1 1
INACTIVE INGREDIENTS: FERRIC OXIDE YELLOW; HYPROMELLOSES; LACTOSE MONOHYDRATE; MAGNESIUM STEARATE; POLYETHYLENE GLYCOL, UNSPECIFIED; POVIDONE; TITANIUM DIOXIDE; STARCH, CORN

Dipyridamole Tablets, USP

PACKAGE LABEL.PRINCIPAL DISPLAY PANEL

NDC 65841-662-01 in bottle of 100 tablets

Dipyridamole Tablets USP, 25 mg

Rx only

100 tablets

ZYDUS

NDC 65841-663-01 in bottle of 100 tablets

Dipyridamole Tablets USP, 50 mg

Rx only

100 tablets

ZYDUS

NDC 65841-664-01 in bottle of 100 tablets

Dipyridamole Tablets USP, 75 mg

Rx only

100 tablets

ZYDUS